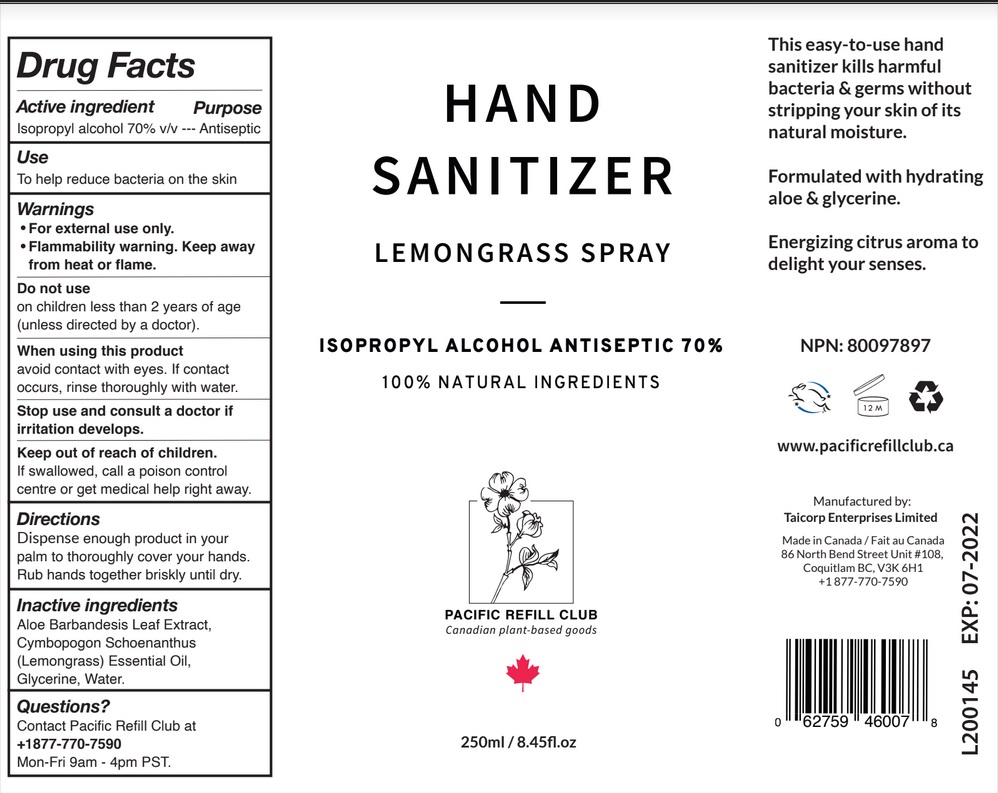 DRUG LABEL: Hand Sanitizer Lemongrass
NDC: 79883-002 | Form: SPRAY
Manufacturer: Taicorp Enterprises Limited
Category: otc | Type: HUMAN OTC DRUG LABEL
Date: 20200802

ACTIVE INGREDIENTS: ISOPROPYL ALCOHOL 70 mL/100 mL
INACTIVE INGREDIENTS: ALOE VERA LEAF; WEST INDIAN LEMONGRASS OIL; GLYCERIN; WATER

Active Ingredient

Isopropyl alcohol 70% v/v

Purpose

Antiseptic

Use

To help reduce bacteria on the skin.

Warnings

For external use only.

Flammability warning: Keep away from heat or flame.

Do not use
on children less than 2 years of age (unless directed by a doctor).

When using this product avoid contact with eyes. If contact occurs, rinse thoroughly with water.

Stop use and consult a doctor if irritation develops.

Keep out of reach of children. If swallowed, get medical help or contact a Poison Control Center right away.

Directions

Dispense enough product in your palm to thoroughly cover your hands. Rub hands together briskly until dry.

Inactive ingredients

Aloe Barbandesis Leaf Extract, Cymbopogon Schoenanthus (Lemongrass) Essential Oil, Glycerine, Water.

Questions?

Contact Pacific Refill Club at
+1 877-770-7590 Mon-Fri 9am - 4pm PST.